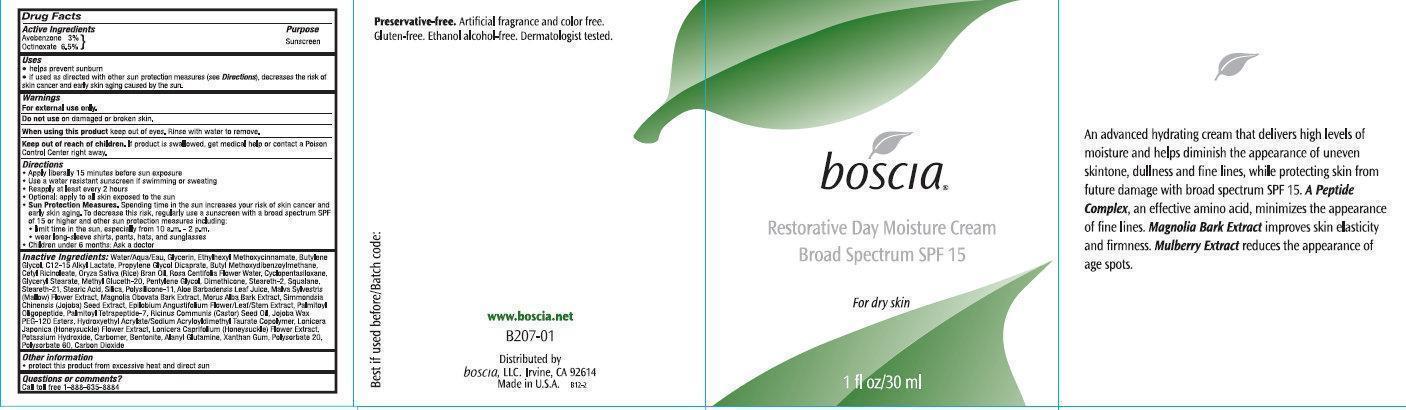 DRUG LABEL: Boscia Restorative Day Moisture Broad Spectrum SPF 15 For Dry Skin
NDC: 76151-217 | Form: CREAM
Manufacturer: Boscia LLC
Category: otc | Type: HUMAN OTC DRUG LABEL
Date: 20231212

ACTIVE INGREDIENTS: AVOBENZONE 30 mg/1 mL; OCTINOXATE 65 mg/1 mL
INACTIVE INGREDIENTS: WATER; GLYCERIN; BUTYLENE GLYCOL; C12-15 ALKYL LACTATE; PROPYLENE GLYCOL DICAPRATE; CETYL RICINOLEATE; RICE BRAN OIL; ROSA CENTIFOLIA FLOWER OIL; CYCLOMETHICONE 5; GLYCERYL MONOSTEARATE; METHYL GLUCETH-20; PENTYLENE GLYCOL; DIMETHICONE; STEARETH-2; SQUALANE; STEARETH-21; STEARIC ACID; SILICON DIOXIDE; ALOE VERA LEAF; MALVA SYLVESTRIS FLOWER; MAGNOLIA OBOVATA BARK; SIMMONDSIA CHINENSIS SEED; EPILOBIUM ANGUSTIFOLIUM FLOWERING TOP; PALMITOYL OLIGOPEPTIDE; PALMITOYL TETRAPEPTIDE-7; CASTOR OIL; SIMMONDSIA CHINENSIS SEED WAX; LONICERA JAPONICA FLOWER; POTASSIUM HYDROXIDE; BENTONITE; ALANYL GLUTAMINE; XANTHAN GUM; POLYSORBATE 20; POLYSORBATE 60; CARBON DIOXIDE

Boscia Restorative Day Moisture Cream Broad Spectrum SPF 15 For Dry Skin

Active Ingredients

Avobenzone 3% Octinoxate 6.5%

Purpose

Sunscreen

Uses

- Helps prevent sunburn.
- If used as directed with other sun protection measures (see), decreases the risk of skin cancer and early skin aging caused by the sun Directions

Warnings

For external use only.

Do not use

on damaged or broken skin.

When using this product

keep out of eyes. Rinse with water to remove.

Keep out of reach of children.

If product is swallowed, get medical help or contact a Poison Control Center right away.

Directions

- Apply liberally 15 minutes before sun exposure.
- Use a water resistant sunscreen if swimming or sweating
- Reapply at least every 2 hours
- Spending time in the sun increases your risk of skin cancer and early skin aging. To decrease this risk, regularly use a sunscreen with a broad spectrum SPF of 15 or higher and other sun protection measures including: Sun Protection Measures.
- Limit time in the sun, especially from 10 a.m. - 2 p.m.
- Wear long-sleeve shirts, pants, hats, and sunglasses
- Children under 6 months: Ask a doctor

Inactive ingredients

Water/Aqua/Eau, Glycerin, Ethylhexyl Methoxycinnamate, Butylene Glycol, C12-15 Alkyl Lactate, Propylene Glycol Dicaprate, Butyl Methoxydibenzoylmethane, Cetyl Ricinoleate, Oryza Sativa (Rice) Bran Oil, Rosa Centifolia Flower Water, Cyclopentasiloxane, Glyceryl Stearate, Mthyl Gluceth-20, Pentylene Glycol, Dimethicone, Steareth-2, Squalane, Steareth-21, Stearic Acid, Silica, Polysilicone-11, Aloe Barbadensis Leaf Juice, Malva Sylvestris (Mallow) Flower Extract, Magnolia Obovata Bark Extract, Morus Alba Bark Extract, Simmondsia Chinensis (Jojoba) Seed Extract, Epilobium Angustifolium Flower/Leaf/Stem Extract, Palmitoyl Oligopeptide, Palmitoyl Tetrapeptide-7, Ricinus Communis (Castor) Seed Oil, Jojoba Wax PEG-120 Esters, Hydroxyethyl Acrylate/Sodium Acryloyldimethyl Taurate Copolymer, Lonicera Japonica (Honeysuckle) Flower Extract, Lonicera Caprifolium (Honeysuckle) Flower Extract, Potassium Hydroxide, Carbomer, Bentonite, Alanyl Glutamine, Xanthan Gum, Polysorbate 20, Polysorbate 60, Carbon Dioxide

Other information

- protect this product from excessive heat and direct sun

Questions or comments?

Call toll free 1-888-635-8884

An advanced hydrating cream that delivers high levels of moisture and helps diminish the appearance of uneven skintone, dullness and fine lines, while protecting skin for future damage with broad spectrum SPF 15. , an effective amino acid, minimizes the appearance of fine lines. improves skin elasticity and firmness. reduces the appearance of age spots. www.boscia.net Distributed by boscia, LLC. Irvine CA 92614 Made in U.S.A. A Peptide Complex Magnolia Bark Extract Mulberry Extract

PACKAGE LABEL

boscia Restorative Day Moisture Cream Broad Spectrum SPF 15 1 fl oz / 30 ml For dry skin